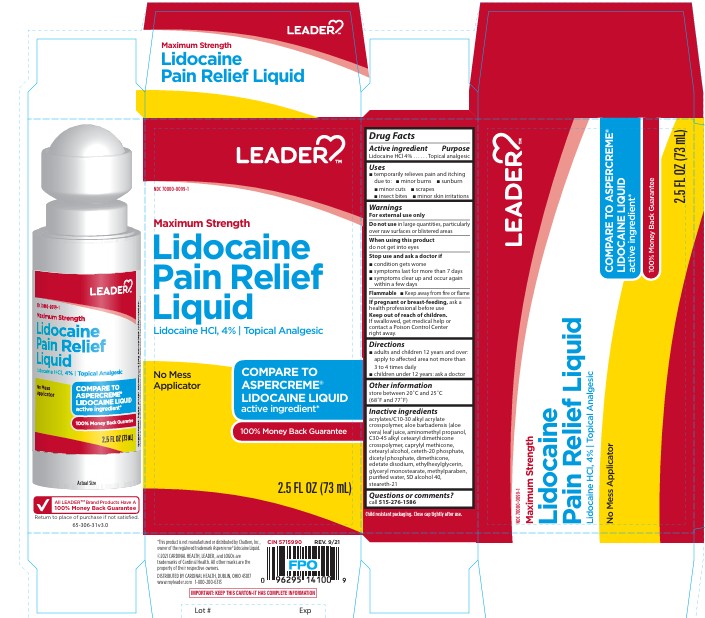 DRUG LABEL: Leader Lidocaine
NDC: 70000-0099 | Form: LIQUID
Manufacturer: CARDINAL HEALTH
Category: otc | Type: HUMAN OTC DRUG LABEL
Date: 20251203

ACTIVE INGREDIENTS: LIDOCAINE HYDROCHLORIDE 4 g/100 mL
INACTIVE INGREDIENTS: GLYCERYL MONOSTEARATE; AMINOMETHYLPROPANOL; CETETH-20 PHOSPHATE; STEARETH-21; ETHYLHEXYLGLYCERIN; METHYLPARABEN; DICETYL PHOSPHATE; DIMETHICONE 350; ALCOHOL; ALOE VERA LEAF; CETEARYL ALCOHOL; EDETATE DISODIUM; WATER; CAPRYLYL METHICONE; ACRYLATES/C10-30 ALKYL ACRYLATE CROSSPOLYMER (60000 MPA.S); C30-45 ALKYL CETEARYL DIMETHICONE CROSSPOLYMER

Leader Lidocaine HCL 4% Roll On

ACTIVE INGREDIENT

Lidocaine HCl 4%

PURPOSE

Topical analgesic

INDICATIONS AND USAGE

temporarily relieves pain and itching due to:

- minor burns
- sunburn
- minor cuts
- scrapes
- insect bites
- minor skin irritations

WARNINGS

For external use only

Do not use in large quantities, particularly over raw surfaces or blistered areas

When using this product do not get into eyes

Stop use and ask a doctor if

- condition gets worse
- symptoms last for more than 7 days
- symptoms clear up and occur again within a few days

GENERAL PRECAUTIONS

Flammable •Keep away from fire or flame

PREGNANCY OR BREAST FEEDING

If pregnant or breast-feeding, ask a health professional before use

Keep out of reach of children. If swallowed, get medical help or contact a Poison Control Center right away.

Directions

- adults and children 12 years and over: apply to affected area not more than 3 to 4 times daily
- children under 12 years: ask a doctor

Other information

store between 20 °C and 25 °C (68 °F and 77 °F)

INACTIVE INGREDIENT

acrylates/C10-30 alkyl acrylate crosspolymer, aloe barbadensis (aloe vera) leaf juice, aminomethyl propanol,
C30-45 alkyl cetearyl dimethicone crosspolymer, caprylyl methicone, cetearyl alcohol, ceteth-20 phosphate, dicetyl phosphate, dimethicone, edetate disodium, ethylhexylglycerin, glyceryl monostearate, methylparaben, purified water, SD alcohol 40, steareth-21

QUESTIONS

call 515-276-1586

PACKAGE LABEL

Leader

NDC 70000-0099-1

Maximum Strength

Lidocaine

Pain Relief

Liquid

Lidocaine HCl, 4% Topical Analgesic

No Mess

Applicator

Compare to

Aspercreme

Lidocaine liquid

active ingredient

100% Money Back Guarantee

2.5 Fl oz (73 mL)